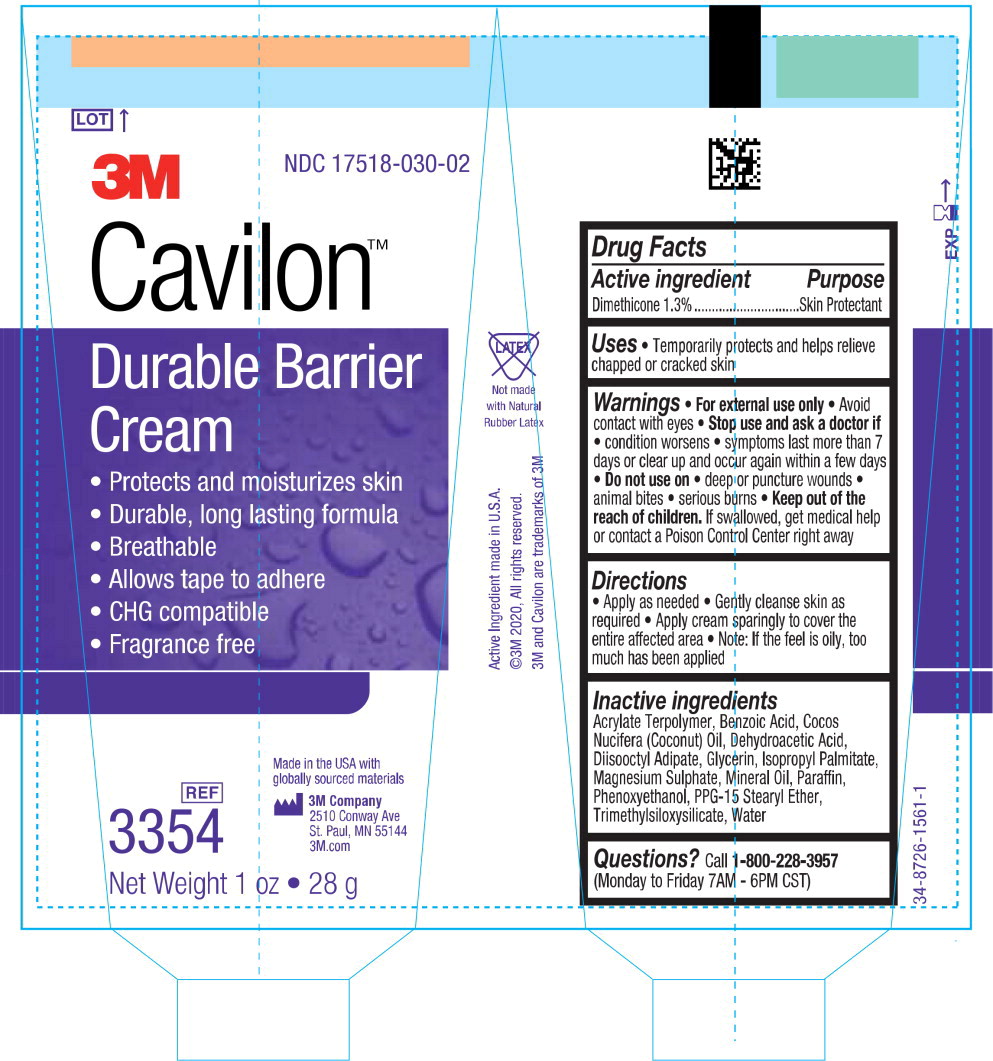 DRUG LABEL: 3M Cavilon Durable Barrier
NDC: 17518-030 | Form: CREAM
Manufacturer: Solventum US LLC
Category: otc | Type: HUMAN OTC DRUG LABEL
Date: 20240801

ACTIVE INGREDIENTS: Dimethicone 13000 mg/1 L
INACTIVE INGREDIENTS: Benzoic Acid; Coconut Oil; Dehydroacetic Acid; Diisooctyl Adipate; Glycerin; Isopropyl Palmitate; Magnesium Sulfate Heptahydrate; Mineral Oil; Paraffin; Phenoxyethanol; PPG-15 Stearyl Ether; Water

3M Cavilon™
Durable Barrier Cream

Drug Facts

Active ingredient

Dimethicone 1.3%

Purpose

Skin Protectant

Uses

- Temporarily protects and helps relieve chapped or cracked skin

Warnings

- For external use only
- Avoid contact with eyes

- Stop use and ask a doctor if
- condition worsens
- symptoms last more than 7 days or clear up and occur again within a few days

- Do not use on
- deep or puncture wounds
- animal bites
- serious burns

KEEP OUT OF REACH OF CHILDREN

- Keep out of the reach of children. If swallowed, get medical help or contact a Poison Control Center right away

Directions

- Apply as needed
- Gently cleanse skin as required
- Apply cream sparingly to cover the entire affected area
- Note: If the feel is oily, too much has been applied

Inactive ingredients

Acrylate Terpolymer, Benzoic Acid, Cocos Nucifera (Coconut) Oil, Dehydroacetic Acid, Diisooctyl Adipate, Glycerin, Isopropyl Palmitate, Magnesium Sulphate, Mineral Oil, Paraffin, Phenoxyethanol, PPG-15 Stearyl Ether, Trimethylsiloxysilicate, Water

Questions?

Call 1-800-228-3957

(Monday to Friday 7AM - 6PM CST)

34-8726-1561-1

Principal Display Panel – 28 g Tube Label

LOT

3M

NDC 17518-030-02

Cavilon™

Durable Barrier

Cream

- Protects and moisturizes skin
- Durable, long lasting formula
- Breathable
- Allows tape to adhere
- CHG compatible
- Fragrance free

Not made with Natural Rubber Latex

Active Ingredient made in U.S.A.

©3M 2020, All rights reserved.

3M and Cavilon are trademarks of 3M

REF

3354

Net Weight 1 oz • 28g

Made in the USA with globally sourced materials

3M Company

2510 Conway Ave

St. Paul, MN 55144

3M.com